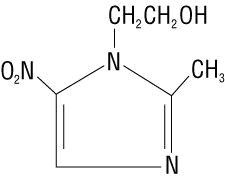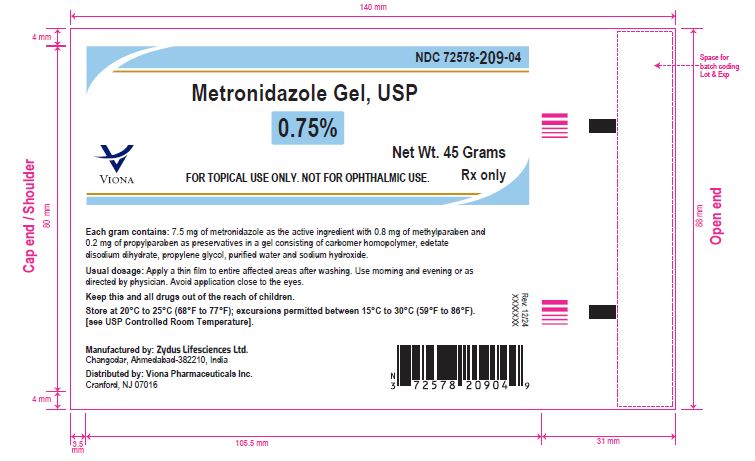 DRUG LABEL: Metronidazole
NDC: 72578-209 | Form: GEL
Manufacturer: Viona Pharmaceuticals Inc
Category: prescription | Type: HUMAN PRESCRIPTION DRUG LABEL
Date: 20260219

ACTIVE INGREDIENTS: METRONIDAZOLE 7.5 mg/1 g
INACTIVE INGREDIENTS: CARBOMER HOMOPOLYMER TYPE C; EDETATE DISODIUM; METHYLPARABEN; PROPYLENE GLYCOL; PROPYLPARABEN; SODIUM HYDROXIDE; WATER

Metronidazole Gel USP, 0.75%

DESCRIPTION

Metronidazole Gel USP, 0.75% contains metronidazole, USP, at a concentration of 7.5 mg per gram (0.75%) in a gel consisting of carbomer homopolymer , edetate disodium dihydrate, methylparaben, propylene glycol, propylparaben, purified water, and sodium hydroxide. Metronidazole is classified therapeutically as an antiprotozoal and antibacterial agent. Chemically, metronidazole is named 2-methyl-5-nitro-1 H-imidazole-1-ethanol and has the following structure:

CLINICAL PHARMACOLOGY

Bioavailability studies on the topical administration of 1 gram of metronidazole Gel (7.5 mg of metronidazole) to the face of 10 rosacea patients showed a maximum serum concentration of 66 nanograms per milliliter in one patient. This concentration is approximately 100 times less than concentrations afforded by a single 250 mg oral tablet. The serum metronidazole concentrations were below the detectable limits of the assay at the majority of time points in all patients. Three of the patients had no detectable serum concentrations of metronidazole at any time point. The mean dose of gel applied during clinical studies was 600 mg which represents 4.5 mg of metronidazole per application. Therefore, under normal usage levels, the formulation affords minimal serum concentrations of metronidazole. The mechanisms by which metronidazole gel acts in the treatment of rosacea are unknown, but appear to include an antiinflammatory effect.

INDICATIONS AND USAGE

Metronidazole Gel is indicated for topical application in the treatment of inflammatory papules and pustules of rosacea.

CONTRAINDICATIONS

Metronidazole Gel is contraindicated in individuals with a history of hypersensitivity to metronidazole, parabens or other ingredients of the formulation.

PRECAUTIONS

General: Metronidazole Gel has been reported to cause tearing of the eyes. Therefore, contact with the eyes should be avoided. If a reaction suggesting local irritation occurs, patients should be directed to use the medication less frequently or discontinue use. Metronidazole is a nitroimidazole and should be used with care in patients with evidence of, or history of blood dyscrasia.

Information for patients: This medication is to be used as directed by the physician. It is for external use only. Avoid contact with the eyes.

Drug Interactions: Oral metronidazole has been reported to potentiate the anticoagulant effect of coumarin and warfarin resulting in a prolongation of prothrombin time. The effect of topical metronidazole on prothrombin time is not known.

Carcinogenesis, mutagenesis, impairment of fertility: Metronidazole has shown evidence of carcinogenic activity in a number of studies involving chronic, oral administration in mice and rats but not in studies involving hamsters.

Metronidazole has shown evidence of mutagenic activity in several in vitro bacterial assay systems. In addition, a dose-response increase in the frequency of micronuclei was observed in mice after intraperitoneal injections and an increase in chromosome aberrations have been reported in patients with Crohn's disease who were treated with 200 mg/day to 1,200 mg/day of metronidazole for 1 month to 24 months. However, no excess chromosomal aberrations in circulating human lympyhocytes have been observed in patients treated for 8 months.

Pregnancy: Teratogenic effects:

There has been no experience to date with the use of metronidazole gel in pregnant patients. Metronidazole crosses the placental barrier and enters the fetal circulation rapidly. No fetotoxicity was observed after oral metronidazole in rats or mice. However, because animal reproduction studies are not always predictive of human response and since oral metronidazole has been shown to be a carcinogen in some rodents, this drug should be used during pregnancy only if clearly needed.

Nursing mothers: After oral administration, metronidazole is secreted in breast milk in concentrations similar to those found in the plasma. Even though metronidazole gel blood levels are significantly lower than those achieved after oral metronidazole, a decision should be made whether to discontinue nursing or to discontinue the drug, taking into account the importance of the drug to the mother

Pediatric use: Safety and effectiveness in pediatric patients have not been established.

ADVERSE REACTIONS

The following adverse experiences have been reported with the topical use of metronidazole: burning, skin irritation, dryness, transient redness, metallic taste, tingling or numbness of extremities and nausea.

To report SUSPECTED ADVERSE REACTIONS, contact Viona Pharmaceuticals Inc.

at 1-888-304-5011 or FDA at 1-800-FDA-1088 or www.fda.gov/medwatch.

DOSAGE AND ADMINISTRATION

Apply and rub in a thin film of metronidazole gel twice daily, morning and evening, to entire affected areas after washing.

Areas to be treated should be cleansed before application of metronidazole gel. Patients may use cosmetics after application of metronidazole gel.

HOW SUPPLIED

Metronidazole Gel USP, 0.75% is supplied in a 45 g tube

NDC 72578-209-04

Storage conditions:

Store at 20° C to 25°C (68°F to 77°F); excursions permitted between 15°C to 30°C (59°F to

86°F). [see USP Controlled Room Temperature].

Keep this and all drugs out of the reach of children.

Manufactured by:

Zydus Lifesciences Ltd.

Changodar, Ahmedabad-382210, India

Distributed by:

Viona Pharmaceuticals Inc.

Cranford, NJ 07016

Rev: 12/24

PACKAGE LABEL.PRINCIPAL DISPLAY PANEL

NDC 72578-209-04

Metronidazole Gel USP, 0.75%

45 grams

Rx

Metronidazole Gel, USP